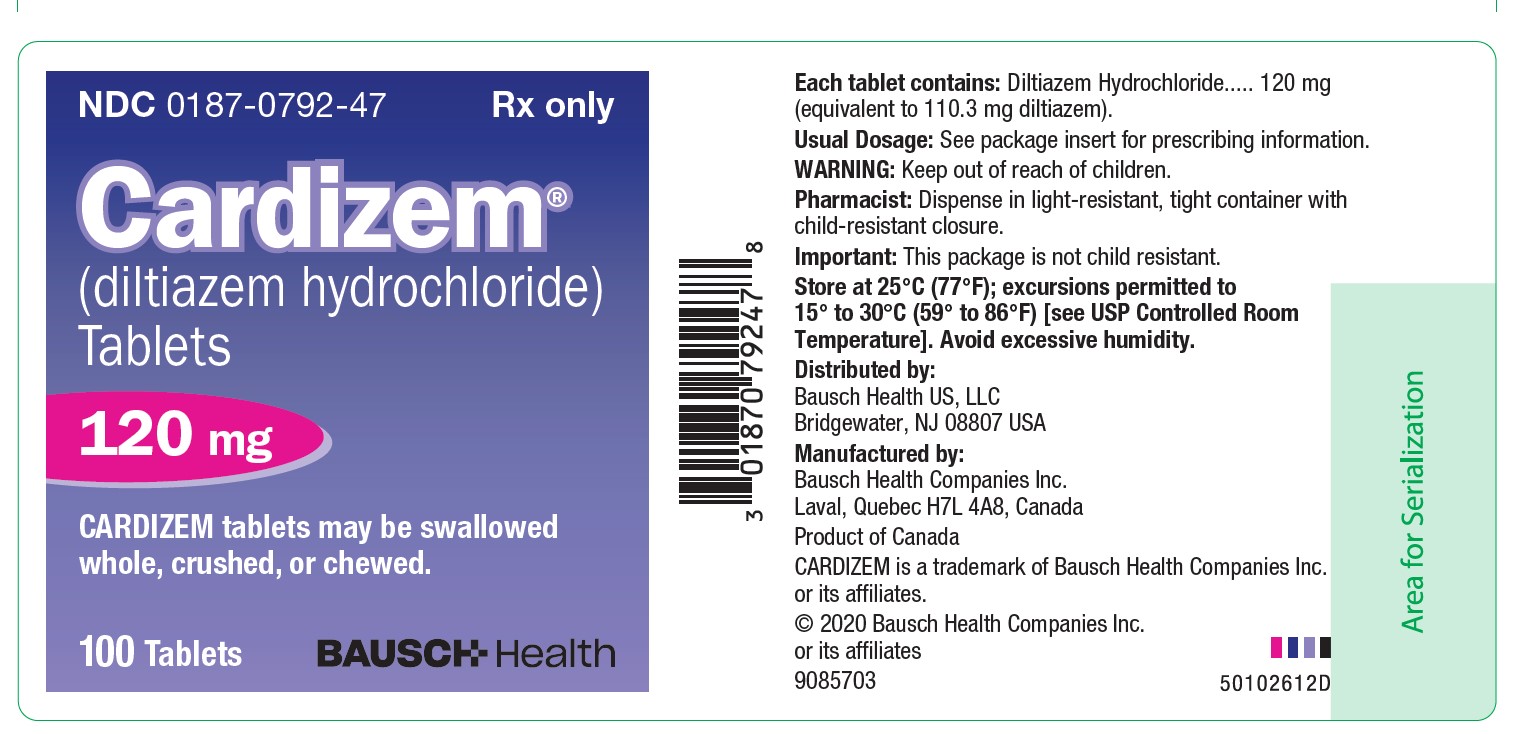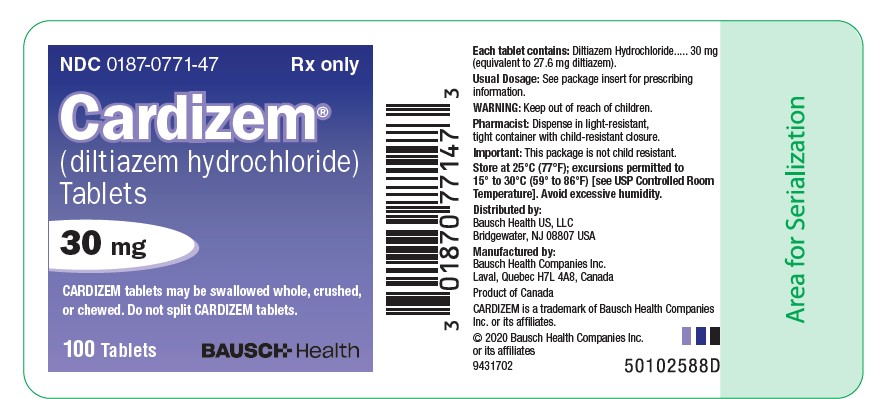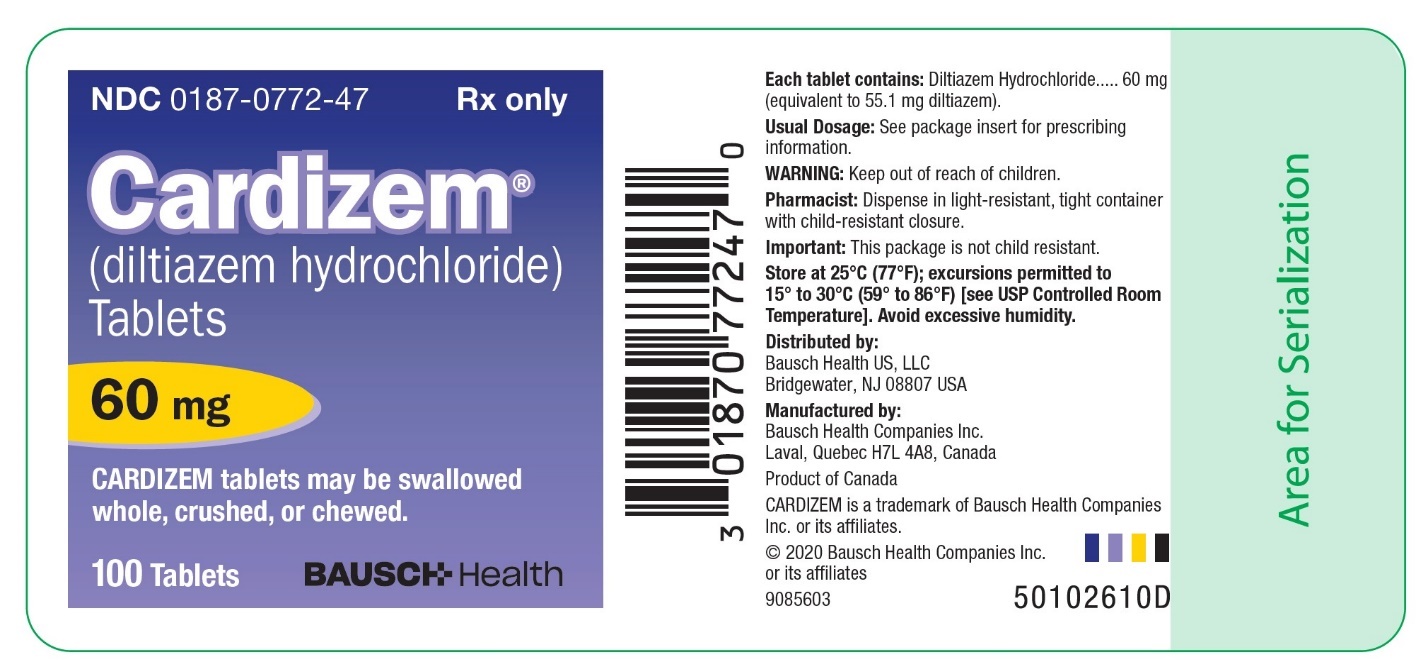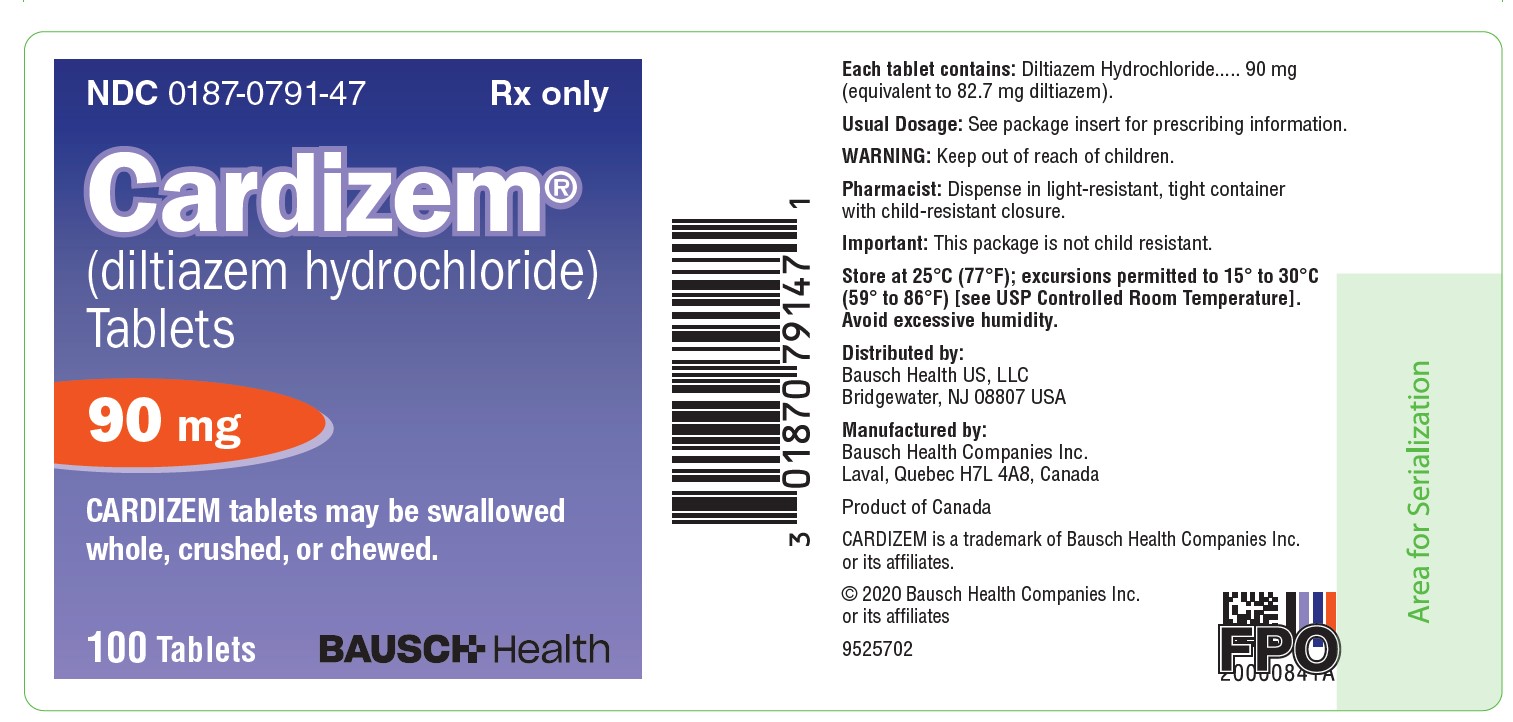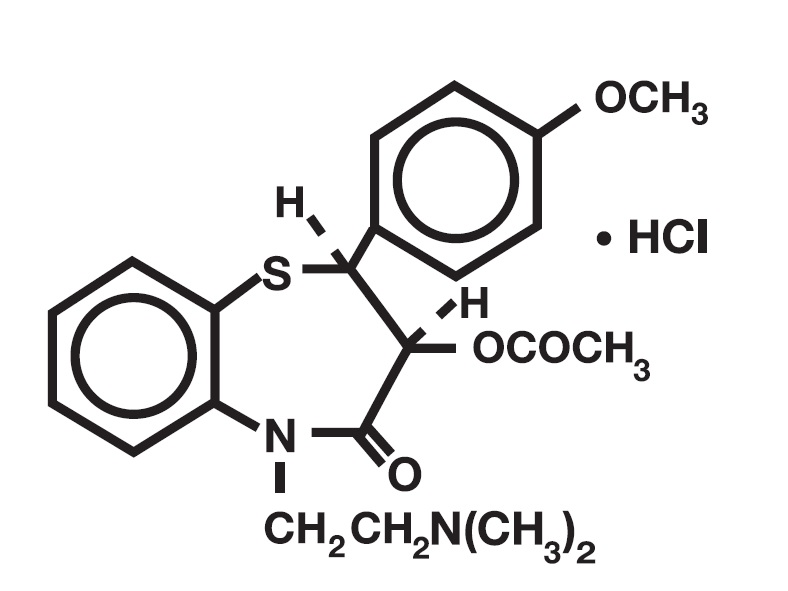 DRUG LABEL: Cardizem
NDC: 0187-0771 | Form: TABLET, COATED
Manufacturer: Bausch Health US LLC
Category: prescription | Type: HUMAN PRESCRIPTION DRUG LABEL
Date: 20250430

ACTIVE INGREDIENTS: DILTIAZEM HYDROCHLORIDE 30 mg/1 1
INACTIVE INGREDIENTS: SILICON DIOXIDE; D&C YELLOW NO. 10; FD&C BLUE NO. 1; LACTOSE, UNSPECIFIED FORM; MAGNESIUM STEARATE; METHYLPARABEN; HYPROMELLOSE, UNSPECIFIED; MICROCRYSTALLINE CELLULOSE; POLYETHYLENE GLYCOL, UNSPECIFIED; HYDROXYPROPYL CELLULOSE, UNSPECIFIED

CARDIZEM®
(diltiazem hydrochloride)
Tablets

DESCRIPTION

CARDIZEM®(diltiazem hydrochloride) is a calcium ion cellular influx inhibitor (slow channel blocker or calcium antagonist). Chemically, diltiazem hydrochloride is 1,5-Benzothiazepin-4(5 H)-one, 3-(acetyloxy)-5-[2-(dimethylamino)ethyl] -2, 3-dihydro-2-(4-methoxyphenyl)-, monohydrochloride,(+)- cis-. The chemical structure is:

Diltiazem hydrochloride is a white to off-white crystalline powder with a bitter taste. It is soluble in water, methanol, and chloroform. It has a molecular weight of 450.98. Each tablet of CARDIZEM contains 30 mg, 60 mg, 90 mg, or 120 mg diltiazem hydrochloride.

Also contains: colloidal silicon dioxide, D&C Yellow #10 Aluminum Lake, FD&C Blue #1 Aluminum Lake (30 mg and 90 mg), FD&C Yellow #6 Aluminum Lake (60 mg and 120 mg), hydroxypropyl cellulose, hypromellose, lactose, magnesium stearate, methylparaben, microcrystalline cellulose, and polyethylene glycol.

For oral administration.

CLINICAL PHARMACOLOGY

The therapeutic benefits achieved with CARDIZEM are believed to be related to its ability to inhibit the influx of calcium ions during membrane depolarization of cardiac and vascular smooth muscle.

Mechanisms of Action

Although precise mechanisms of its antianginal actions are still being delineated, CARDIZEM is believed to act in the following ways:

- Angina Due to Coronary Artery Spasm:CARDIZEM has been shown to be a potent dilator of coronary arteries both epicardial and subendocardial. Spontaneous and ergonovine-induced coronary artery spasms are inhibited by CARDIZEM.
- Exertional Angina:CARDIZEM has been shown to produce increases in exercise tolerance, probably due to its ability to reduce myocardial oxygen demand. This is accomplished via reductions in heart rate and systemic blood pressure at submaximal and maximal exercise workloads.

In animal models, diltiazem interferes with the slow inward (depolarizing) current in excitable tissue. It causes excitation-contraction uncoupling in various myocardial tissues without changes in the configuration of the action potential. Diltiazem produces relaxation of coronary vascular smooth muscle and dilation of both large and small coronary arteries at drug levels which cause little or no negative inotropic effect. The resultant increases in coronary blood flow (epicardial and subendocardial) occur in ischemic and nonischemic models and are accompanied by dose-dependent decreases in systemic blood pressure and decreases in peripheral resistance.

Hemodynamic and Electrophysiologic Effects

Like other calcium antagonists, diltiazem decreases sinoatrial and atrioventricular conduction in isolated tissues and has a negative inotropic effect in isolated preparations. In the intact animal, prolongation of the AH interval can be seen at higher doses.

In man, diltiazem prevents spontaneous and ergonovine-provoked coronary artery spasm. It causes a decrease in peripheral vascular resistance and a modest fall in blood pressure, and in exercise tolerance studies in patients with ischemic heart disease, reduces the heart rate-blood pressure product for any given workload. Studies to date, primarily in patients with good ventricular function, have not revealed evidence of a negative inotropic effect; cardiac output, ejection fraction, and left ventricular end-diastolic pressure have not been affected. There are as yet few data on the interaction of diltiazem and beta-blockers. Resting heart rate is usually unchanged or slightly reduced by diltiazem.

Intravenous diltiazem in doses of 20 mg prolongs AH conduction time and AV node functional and effective refractory periods approximately 20%. In a study involving single oral doses of 300 mg of CARDIZEM in six normal volunteers, the average maximum PR prolongation was 14% with no instances of greater than first-degree AV block. Diltiazem-associated prolongation of the AH interval is not more pronounced in patients with first-degree heart block. In patients with sick sinus syndrome, diltiazem significantly prolongs sinus cycle length (up to 50% in some cases).

Chronic oral administration of CARDIZEM in doses of up to 240 mg/day has resulted in small increases in PR interval but has not usually produced abnormal prolongation.

Pharmacokinetics and Metabolism

Diltiazem is well absorbed from the gastrointestinal tract and is subject to an extensive first-pass effect, giving an absolute bioavailability (compared to intravenous dosing) of about 40%. CARDIZEM undergoes extensive metabolism in which 2% to 4% of the unchanged drug appears in the urine. In vitro binding studies show CARDIZEM is 70% to 80% bound to plasma proteins. Competitive in vitro ligand binding studies have also shown CARDIZEM binding is not altered by therapeutic concentrations of digoxin, hydrochlorothiazide, phenylbutazone, propranolol, salicylic acid, or warfarin. The plasma elimination half-life following single or multiple drug administration is approximately 3.0 to 4.5 hours. Desacetyl diltiazem is also present in the plasma at levels of 10% to 20% of the parent drug and is 25% to 50% as potent as a coronary vasodilator as diltiazem. Minimum therapeutic plasma levels of CARDIZEM appear to be in the range of 50 to 200 ng/mL. There is a departure from linearity when dose strengths are increased. A study that compared patients with normal hepatic function to patients with cirrhosis found an increase in half-life and a 69% increase in AUC (area-under-the-plasma concentration vs. time curve) in the hepatically impaired patients. A single study in nine patients with severely impaired renal functions showed no difference in the pharmacokinetic profile of diltiazem as compared to patients with normal renal function.

CARDIZEM Tablets:Diltiazem is absorbed from the tablet formulation to about 98% of a reference solution. Single oral doses of 30 to 120 mg of CARDIZEM tablets result in detectable plasma levels within 30 to 60 minutes and peak plasma levels 2 to 4 hours after drug administration. As the dose of CARDIZEM tablets is increased from a daily dose of 120 mg (30 mg QID) to 240 mg (60 mg QID) daily, there is an increase in area-under-the-curve of 2.3 times. When the dose is increased from 240 mg to 360 mg daily, there is an increase in area-under-the-curve of 1.8 times.

INDICATIONS AND USAGE

CARDIZEM is indicated for the management of chronic stable angina and angina due to coronary artery spasm.

CONTRAINDICATIONS

CARDIZEM is contraindicated in:

- Patients with sick sinus syndrome except in the presence of a functioning ventricular pacemaker
- Patients with second- or third-degree AV block except in the presence of a functioning ventricular pacemaker
- Patients with hypotension (less than 90 mm Hg systolic)
- Patients who have demonstrated hypersensitivity to the drug
- Patients with acute myocardial infarction and pulmonary congestion documented by x-ray on admission

WARNINGS

1. Cardiac Conduction:CARDIZEM prolongs AV node refractory periods without significantly prolonging sinus node recovery time, except in patients with sick sinus syndrome. This effect may rarely result in abnormally slow heart rates (particularly in patients with sick sinus syndrome) or second- or third-degree AV block (six of 1243 patients for 0.48%). Concomitant use of diltiazem with beta-blockers or digitalis may result in additive effects on cardiac conduction. A patient with Prinzmetal’s angina developed periods of asystole (2 to 5 seconds) after a single dose of 60 mg of diltiazem (see ADVERSE REACTIONS).
2. Congestive Heart Failure:Although diltiazem has a negative inotropic effect in isolated animal tissue preparations, hemodynamic studies in humans with normal ventricular function have not shown a reduction in cardiac index nor consistent negative effects on contractility (dP/dt). Experience with the use of CARDIZEM alone or in combination with beta-blockers in patients with impaired ventricular function is very limited. Caution should be exercised when using the drug in such patients.
3. Hypotension:Decreases in blood pressure associated with CARDIZEM therapy may occasionally result in symptomatic hypotension.
4. Acute Hepatic Injury:In rare instances, significant elevations in enzymes such as alkaline phosphatase, LDH, SGOT, SGPT, and other phenomena consistent with acute hepatic injury have been noted. These reactions have been reversible upon discontinuation of drug therapy. The relationship to CARDIZEM is uncertain in most cases, but probable in some (see PRECAUTIONS).

PRECAUTIONS

General

CARDIZEM (diltiazem hydrochloride) is extensively metabolized by the liver and excreted by the kidneys and in bile. As with any drug given over prolonged periods, laboratory parameters of renal and hepatic function should be monitored at regular intervals. The drug should be used with caution in patients with impaired renal or hepatic function. In subacute and chronic dog and rat studies designed to produce toxicity, high doses of diltiazem were associated with hepatic damage. In special subacute hepatic studies, oral doses of 125 mg/kg and higher in rats were associated with histological changes in the liver, which were reversible when the drug was discontinued. In dogs, doses of 20 mg/kg were also associated with hepatic changes; however, these changes were reversible with continued dosing. Dermatological events (see ADVERSE REACTIONS) may be transient and may disappear despite continued use of CARDIZEM. However, skin eruptions progressing to erythema multiforme and/or exfoliative dermatitis have also been infrequently reported. Should a dermatologic reaction persist, the drug should be discontinued.

Drug Interactions

Due to the potential for additive effects, caution and careful titration are warranted in patients receiving CARDIZEM concomitantly with any agents known to affect cardiac contractility and/or conduction (see WARNINGS).

Pharmacologic studies indicate that there may be additive effects in prolonging AV conduction when using beta-blockers or digitalis concomitantly with CARDIZEM (see WARNINGS).

Diltiazem is both a substrate and an inhibitor of the Pg-p and cytochrome P450 3A4 enzyme system which may affect exposure to diltiazem and concomitant drugs metabolized by those pathways. Patients with renal and/or hepatic impairment may be particularly at risk of exposure changes.

Anesthetics:The depression of cardiac contractility, conductivity, and automaticity, as well as the vascular dilation associated with anesthetics, may be potentiated by calcium channel blockers. When used concomitantly, anesthetics and calcium blockers should be titrated carefully.

Benzodiazepines:Studies showed that diltiazem increased the AUC of midazolam and triazolam by 3- to 4-fold and the Cmaxby 2-fold, compared to placebo. The elimination half-life of midazolam and triazolam also increased (1.5- to 2.5-fold) during coadministration with diltiazem. These pharmacokinetic effects seen during diltiazem coadministration can result in increased clinical effects (e.g., prolonged sedation) of both midazolam and triazolam.

Beta-blockers:Controlled and uncontrolled domestic studies suggest that concomitant use of CARDIZEM and beta-blockers is usually well tolerated. Available data are not sufficient, however, to predict the effects of concomitant treatment, particularly in patients with left ventricular dysfunction or cardiac conduction abnormalities.

Administration of CARDIZEM (diltiazem hydrochloride) concomitantly with propranolol in five normal volunteers resulted in increased propranolol levels in all subjects, and bioavailability of propranolol was increased approximately 50%. In vitro, propranolol appears to be displaced from its binding sites by diltiazem. If combination therapy is initiated or withdrawn in conjunction with propranolol, an adjustment in the propranolol dose may be warranted (see WARNINGS).

Buspirone:In nine healthy subjects, diltiazem significantly increased the mean buspirone AUC 5.5-fold and Cmax4.1-fold compared to placebo. The T1/2and Tmaxof buspirone were not significantly affected by diltiazem. Enhanced effects and increased toxicity of buspirone may be possible during concomitant administration with diltiazem. Subsequent dose adjustments may be necessary during coadministration and should be based on clinical assessment.

Carbamazepine:Concomitant administration of diltiazem with carbamazepine has been reported to result in elevated serum levels of carbamazepine (40% to 72% increase) resulting in toxicity in some cases. Patients receiving these drugs concurrently should be monitored for a potential drug interaction.

Cimetidine:A study in six healthy volunteers has shown a significant increase in peak diltiazem plasma levels (58%) and area-under-the-curve (53%) after a 1-week course of cimetidine at 1200 mg per day and a single dose of diltiazem 60 mg. Ranitidine produced smaller, nonsignificant increases. The effect may be mediated by cimetidine’s known inhibition of hepatic cytochrome P450, the enzyme system responsible for the first-pass metabolism of diltiazem. Patients currently receiving diltiazem therapy should be carefully monitored for a change in pharmacological effect when initiating and discontinuing therapy with cimetidine. An adjustment in the diltiazem dose may be warranted.

Clonidine:Sinus bradycardia resulting in hospitalization and pacemaker insertion has been reported in association with the use of clonidine concurrently with diltiazem. Monitor heart rate in patients receiving concomitant diltiazem and clonidine.

Cyclosporine:A pharmacokinetic interaction between diltiazem and cyclosporine has been observed during studies involving renal and cardiac transplant patients. In renal and cardiac transplant recipients, a reduction of cyclosporine trough dose ranging from 15% to 48% was necessary to maintain concentrations similar to those seen prior to the addition of diltiazem. If these agents are to be administered concurrently, cyclosporine concentrations should be monitored, especially when diltiazem therapy is initiated, adjusted, or discontinued. The effect of cyclosporine on diltiazem plasma concentrations has not been evaluated.

Digitalis:Administration of CARDIZEM with digoxin in 24 healthy male subjects increased plasma digoxin concentrations approximately 20%. Another investigator found no increase in digoxin levels in 12 patients with coronary artery disease. Since there have been conflicting results regarding the effect of digoxin levels, it is recommended that digoxin levels be monitored when initiating, adjusting, and discontinuing CARDIZEM therapy to avoid possible over- or under-digitalization (see WARNINGS).

Ivabradine:Concurrent use of diltiazem increases exposure to ivabradine and may exacerbate bradycardia and conduction disturbances. Avoid concomitant use of ivabradine and diltiazem.

Quinidine:Diltiazem significantly increases the AUC(0→∞)of quinidine by 51%, T1/2by 36%, and decreases its CLoralby 33%. Monitoring for quinidine adverse effects may be warranted and the dose adjusted accordingly.

Rifampin:Coadministration of rifampin with diltiazem lowered the diltiazem plasma concentrations to undetectable levels. Coadministration of diltiazem with rifampin or any known CYP3A4 inducer should be avoided when possible, and alternative therapy considered.

Statins:Diltiazem is an inhibitor of CYP3A4 and has been shown to increase significantly the AUC of some statins. The risk of myopathy and rhabdomyolysis with statins metabolized by CYP3A4 may be increased with concomitant use of diltiazem. When possible, use a non-CYP3A4-metabolized statin together with diltiazem; otherwise, dose adjustments for both diltiazem and the statin should be considered along with close monitoring for signs and symptoms of any statin-related adverse events.

In a healthy volunteer crossover study (N=10), coadministration of a single 20 mg dose of simvastatin at the end of a 14-day regimen with 120 mg BID diltiazem SR resulted in a 5-fold increase in mean simvastatin AUC versus simvastatin alone. Subjects with increased average steady-state exposures of diltiazem showed a greater fold increase in simvastatin exposure. Computer-based simulations showed that at a daily dose of 480 mg of diltiazem, an 8- to 9-fold mean increase in simvastatin AUC can be expected. If coadministration of simvastatin with diltiazem is required, limit the daily doses of simvastatin to 10 mg and diltiazem to 240 mg.

In a ten-subject randomized, open label, 4-way crossover study, coadministration of diltiazem (120 mg BID diltiazem SR for 2 weeks) with a single 20 mg dose of lovastatin resulted in 3- to 4-fold increase in mean lovastatin AUC and Cmaxversus lovastatin alone. In the same study, there was no significant change in 20 mg single dose pravastatin AUC and Cmaxduring diltiazem coadministration. Diltiazem plasma levels were not significantly affected by lovastatin or pravastatin.

Carcinogenesis, Mutagenesis, Impairment of Fertility

A 24-month study in rats and a 21-month study in mice showed no evidence of carcinogenicity. There was also no mutagenic response in in vitrobacterial tests. No intrinsic effect on fertility was observed in rats.

Pregnancy

Reproduction studies have been conducted in mice, rats, and rabbits. Administration of doses ranging from five to ten times greater (on a mg/kg basis) than the daily recommended therapeutic dose has resulted in embryo and fetal lethality. These doses, in some studies, have been reported to cause skeletal abnormalities. In the perinatal/postnatal studies, there was some reduction in early individual pup weights and survival rates. There was an increased incidence of stillbirths at doses of 20 times the human dose or greater.

There are no well-controlled studies in pregnant women; therefore, use CARDIZEM in pregnant women only if the potential benefit justifies the potential risk to the fetus.

Nursing Mothers

Diltiazem is excreted in human milk. One report suggests that concentrations in breast milk may approximate serum levels. If use of CARDIZEM is deemed essential, an alternative method of infant feeding should be instituted.

Pediatric Use

Safety and effectiveness in pediatric patients have not been established.

Geriatric Use

Clinical studies of diltiazem did not include sufficient numbers of subjects aged 65 and over to determine whether they respond differently from younger subjects. Other reported clinical experience has not identified differences in responses between the elderly and younger patients. In general, dose selection for an elderly patient should be cautious, usually starting at the low end of the dosing range, reflecting the greater frequency of decreased hepatic, renal, or cardiac function, and of concomitant disease or other drug therapy.

Information for Patients

30 mg – CARDIZEM tablets may be swallowed whole, crushed, or chewed. Do not split CARDIZEM tablets.

60 mg, 90 mg, and 120 mg – CARDIZEM tablets may be swallowed whole, crushed, or chewed.

ADVERSE REACTIONS

Serious adverse reactions have been rare in studies carried out to date, but it should be recognized that patients with impaired ventricular function and cardiac conduction abnormalities usually have been excluded.

In domestic placebo-controlled angina trials, the incidence of adverse reactions reported during CARDIZEM therapy was not greater than that reported during placebo therapy.

The following represent occurrences observed in clinical studies of angina patients. In many cases, the relationship to CARDIZEM has not been established. The most common occurrences from these studies, as well as their frequency of presentation, are edema (2.4%), headache (2.1%), nausea (1.9%), dizziness (1.5%), rash (1.3%), and asthenia (1.2%). In addition, the following events were reported infrequently (less than 1%):

Cardiovascular:Angina, arrhythmia, AV block (first-degree), AV block (second- or third-degree – see WARNINGS, Cardiac Conduction), bradycardia, bundle branch block, congestive heart failure, ECG abnormality, flushing, hypotension, palpitations, syncope, tachycardia, ventricular extrasystoles

Nervous System:Abnormal dreams, amnesia, depression, gait abnormality, hallucinations, insomnia, nervousness, paresthesia, personality change, somnolence, tremor

Gastrointestinal:Anorexia, constipation, diarrhea, dysgeusia, dyspepsia, mild elevations of alkaline phosphatase, SGOT, SGPT, and LDH (see WARNINGS, Acute Hepatic Injury), thirst, vomiting, weight increase.

Dermatological:Petechiae, photosensitivity, pruritus, urticaria

Other:Amblyopia, CPK elevation, dry mouth, dyspnea, epistaxis, eye irritation, hyperglycemia, hyperuricemia, impotence, muscle cramps, nasal congestion, nocturia, osteoarticular pain, polyuria, sexual difficulties, tinnitus

The following postmarketing events have been reported infrequently in patients receiving CARDIZEM: acute generalized exanthematous pustulosis, allergic reactions, alopecia, angioedema (including facial or periorbital edema), asystole, erythema multiforme (including Stevens-Johnson syndrome, toxic epidermal necrolysis), extrapyramidal symptoms, gingival hyperplasia, hemolytic anemia, increased bleeding time, leukopenia, photosensitivity (including lichenoid keratosis and hyperpigmentation at sun-exposed skin areas), purpura, retinopathy, myopathy, and thrombocytopenia. There have been observed cases of a generalized rash, some characterized as leukocytoclastic vasculitis. In addition, events such as myocardial infarction have been observed, which are not readily distinguishable from the natural history of the disease in these patients. A definitive cause and effect relationship between these events and CARDIZEM therapy cannot yet be established. Exfoliative dermatitis (proven by rechallenge) has also been reported.

To report SUSPECTED ADVERSE REACTIONS, contact Bausch Health US, LLC at 1-800-321-4576 or FDA at 1-800-FDA-1088 or www.fda.gov/medwatch.

OVERDOSAGE

The oral LD50s in mice and rats range from 415 to 740 mg/kg and from 560 to 810 mg/kg, respectively. The intravenous LD50s in these species were 60 and 38 mg/kg, respectively. The oral LD50in dogs is considered to be in excess of 50 mg/kg, while lethality was seen in monkeys at 360 mg/kg.

The toxic dose in man is not known. Due to extensive metabolism, blood levels after a standard dose of diltiazem can vary over tenfold, limiting the usefulness of blood levels in overdose cases.

There have been reports of diltiazem overdose in amounts ranging from <1 g to 18 g. Of cases with known outcome, most patients recovered and in cases with a fatal outcome, the majority involved multiple drug ingestion.

Events observed following diltiazem overdose included bradycardia, hypotension, heart block, and cardiac failure. Most reports of overdose described some supportive medical measure and/or drug treatment. Bradycardia frequently responded favorably to atropine, as did heart block, although cardiac pacing was also frequently utilized to treat heart block. Fluids and vasopressors were used to maintain blood pressure, and in cases of cardiac failure, inotropic agents were administered. In addition, some patients received treatment with ventilatory support, gastric lavage, activated charcoal, and/or intravenous calcium.

The effectiveness of intravenous calcium administration to reverse the pharmacological effects of diltiazem overdose has been inconsistent. In a few reported cases, overdose with calcium channel blockers associated with hypotension and bradycardia that was initially refractory to atropine became more responsive to atropine after the patients received intravenous calcium. In some cases intravenous calcium has been administered (1 g calcium chloride or 3 g calcium gluconate) over 5 minutes and repeated every 10 to 20 minutes as necessary. Calcium gluconate has also been administered as a continuous infusion at a rate of 2 g per hour for 10 hours. Infusions of calcium for 24 hours or more may be required. Patients should be monitored for signs of hypercalcemia.

In the event of overdose or exaggerated response, appropriate supportive measures should be employed in addition to gastrointestinal decontamination. Diltiazem does not appear to be removed by peritoneal or hemodialysis. Limited data suggest that plasmapheresis or charcoal hemoperfusion may hasten diltiazem elimination following overdose. Based on the known pharmacological effects of diltiazem and/or reported clinical experiences, the following measures may be considered:

Bradycardia:Administer atropine (0.60 to 1.0 mg). If there is no response to vagal blockade, administer isoproterenol cautiously.

High-Degree AV Block:Treat as for bradycardia above. Fixed high-degree AV block should be treated with cardiac pacing.

Cardiac Failure:Administer inotropic agents (isoproterenol, dopamine, or dobutamine) and diuretics.

Hypotension:Vasopressors (e.g., dopamine or norepinephrine).

Actual treatment and dosage should depend on the severity of the clinical situation and the judgment and experience of the treating physician.

DOSAGE AND ADMINISTRATION

Exertional Angina Pectoris Due to Atherosclerotic Coronary Artery Disease or Angina Pectoris at Rest Due to Coronary Artery Spasm:Dosage must be adjusted to each patient’s needs. Starting with 30 mg four times daily, before meals and at bedtime, dosage should be increased gradually (given in divided doses three or four times daily) at 1- to 2-day intervals until optimum response is obtained. Although individual patients may respond to any dosage level, the average optimum dosage range appears to be 180 to 360 mg/day. There are no available data concerning dosage requirements in patients with impaired renal or hepatic function. If the drug must be used in such patients, titration should be carried out with particular caution.

Concomitant Use with Other Cardiovascular Agents

- Sublingual NTGmay be taken as required to abort acute anginal attacks during CARDIZEM (diltiazem hydrochloride) therapy.
- Prophylactic Nitrate Therapy.CARDIZEM may be safely coadministered with short- and long-acting nitrates, but there have been no controlled studies to evaluate the antianginal effectiveness of this combination.
- Beta-blockers.(see WARNINGSand PRECAUTIONS.)
- 30 mg – CARDIZEM tablets may be swallowed whole, crushed, or chewed. Do not split CARDIZEM tablets.
- 60 mg, 90 mg, and 120 mg – CARDIZEM tablets may be swallowed whole, crushed, or chewed.

HOW SUPPLIED

CARDIZEM 30 mg tablets are supplied in bottles of 100 (NDC 0187-0771-47) and 500 (NDC 0187-0771-55). Each light green, round tablet is engraved with MARION on one side and 1771 on the other.

CARDIZEM 60 mg scored tablets are supplied in bottles of 100 (NDC 0187-0772-47) and 500 (NDC 0187-0772-55). Each light yellow, round tablet is engraved with MARION on one side and 1772 on the other.

CARDIZEM 90 mg scored tablets are supplied in bottles of 100 (NDC 0187-0791-47) and 500 (NDC 0187-0791-55). Each light green, capsule-shaped tablet is engraved with CARDIZEM on one side and 90 mg on the other.

CARDIZEM 120 mg scored tablets are supplied in bottles of 100 (NDC 0187-0792-47). Each yellow, capsule-shaped tablet is engraved with CARDIZEM on one side and 120 mg on the other.

Store at 25°C (77°F); excursions permitted to 15° to 30°C (59° to 86°F) [see USP Controlled Room Temperature]. Avoid excessive humidity.

Distributed by:
Bausch Health US, LLC
Bridgewater, NJ 08807 USA

Manufactured by:
Bausch Health Companies Inc.
Laval, Quebec H7L 4A8, Canada

CARDIZEM is a trademark of Bausch Health Companies Inc. or its affiliates.

© 2025 Bausch Health Companies Inc. or its affiliates

Rev. 4/2025

9411005

PRINCIPAL DISPLAY PANEL - 120 mg Tablet Bottle Label

NDC0187-0792-47

Rx only

Cardizem®
(diltiazem hydrochloride)
Tablets

120 mg

CARDIZEM tablets may be swallowed whole, crushed, or chewed.

100 Tablets

BAUSCH Health

Package/Label Display Panel – 90 mg Tablet Bottle Label

NDC0187-0791-47

Rx only

Cardizem®
(diltiazem hydrochloride)
Tablets

90 mg

CARDIZEM tablets may be swallowed whole, crushed, or chewed.

100 Tablets

BAUSCH Health

PRINCIPAL DISPLAY PANEL - 30 mg Tablet Bottle Label

NDC0187-0771-47

Rx only

Cardizem®
(diltiazem hydrochloride)
Tablets

30 mg

CARDIZEM tablets may be swallowed whole, crushed, or chewed. Do not split CARDIZEM tablets.

100 Tablets

BAUSCH Health

PRINCIPAL DISPLAY PANEL - 60 mg Tablet Bottle Label

NDC0187-0772-47

Rx only

Cardizem®
(diltiazem hydrochloride)
Tablets

60 mg

CARDIZEM tablets may be swallowed whole, crushed, or chewed.

100 Tablets

BAUSCH Health